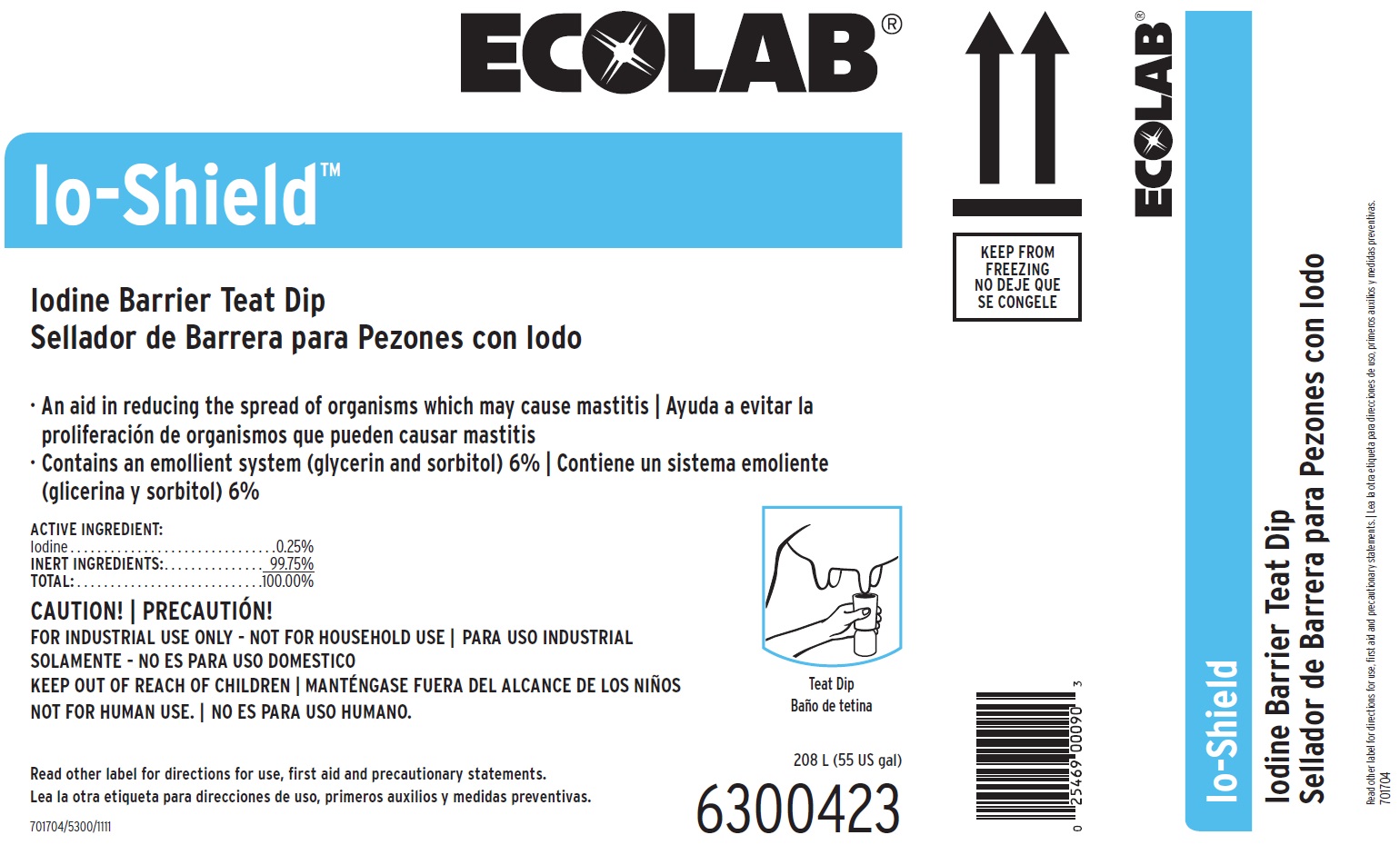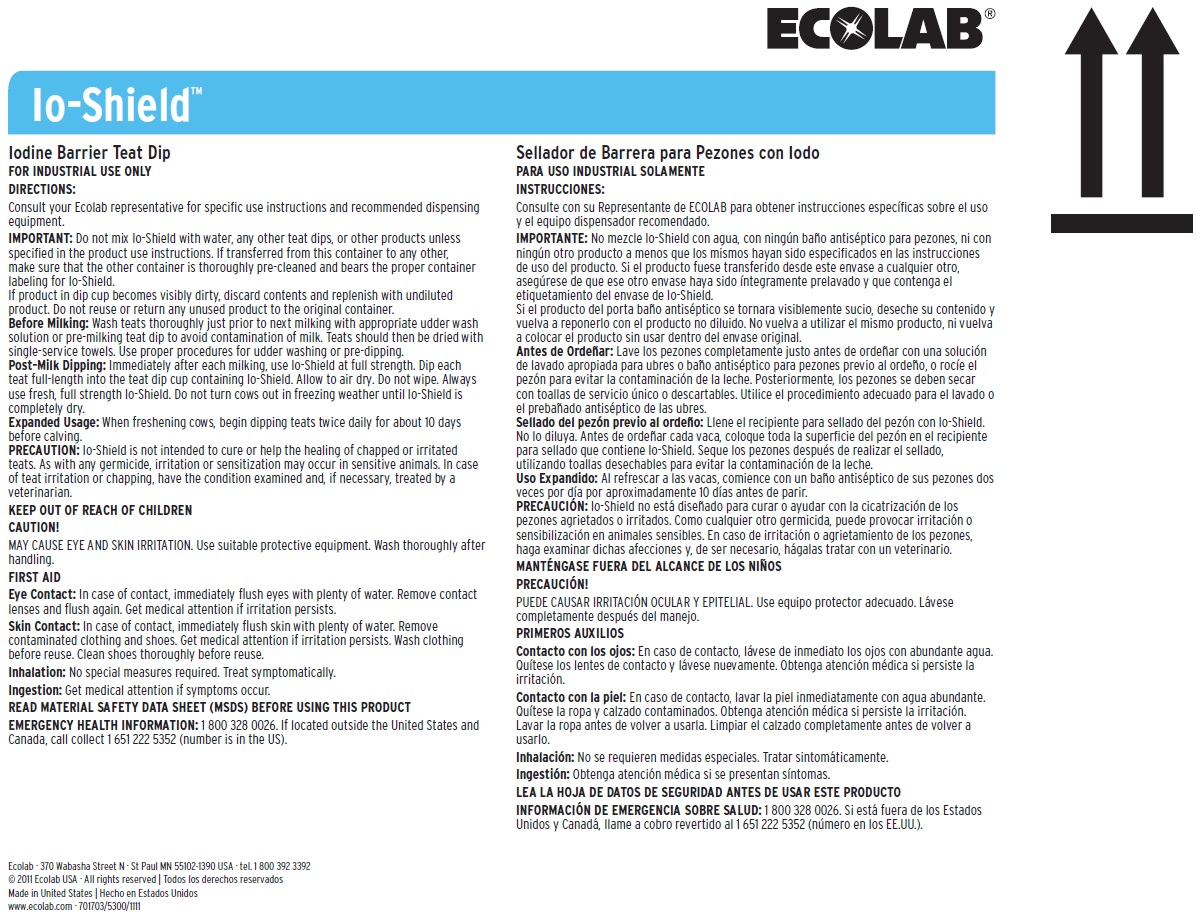 DRUG LABEL: IO-Shield
NDC: 47593-132 | Form: SOLUTION
Manufacturer: Ecolab Inc.
Category: animal | Type: OTC ANIMAL DRUG LABEL
Date: 20250725

ACTIVE INGREDIENTS: IODINE 2.5 mg/1 mL
INACTIVE INGREDIENTS: WATER; SORBITOL; GLYCERIN

SAFE HANDLING WARNING

FOR INDUSTRIAL USE ONLY

KEEP OUT OF REACH OF CHILDREN

NOT FOR HUMAN USE

Read other label for directions for use, first aid and precautionary statements.

CAUTION!

MAY CAUSE EYE AND SKIN IRRITATION. Use suitable protective equipment. Wash thoroughly after handling.

READ MATERIAL SAFETY DATA SHEET (MSDS) BEFORE USING THIS PRODUCT

EMERGENCY HEALTH INFORMATION: 1 800 328 0026. If located outside the United States and Canada, call collect 1 651 222 5352 (number is in the US).

DIRECTIONS:

Consult your Ecolab representative for specific use instructions and recommended dispensing equipment.

IMPORTANT: Do not mix Io-Shield with water, any other teat dips, or other products unless specified in the product use instructions. If transferred from this container to any other, make sure that the other container is thoroughly pre-cleaned and bears the proper container labeling for Io-Shield.

If product in dip cup becomes visibly dirty, discard contents and replenish with undiluted product. Do not reuse or return any unused product to the original container.

Before Milking: Wash teats thoroughly just prior to next milking with appropriate udder wash solution or pre-milking teat dip to avoid contamination of milk. Teats should then be dried with single-service towels. Use proper procedures for udder washing or pre-dipping.

Post-Milk Dipping: Immediately after each milking, use Io-Shield at full strength. Dip each teat full-length into the teat dip cup containing Io-Shield. Allow to air dry. Do not wipe. Always use fresh, full strength Io-Shield. Do not turn cows out in freezing weather until Io-Shield is completely dry.

Expanded Usage: When freshening cows, begin dipping teats twice daily for about 10 days before calving.

PRECAUTION: Io-Shield is not intended to cure or help the healing of chapped or irritated teats. As with any germicide, irritation or sensitization may occur in sensitive animals. In case of teat irritation or chapping, have the condition examined and, if necessary, treated by a veterinarian.

OTHER SAFETY INFORMATION

FIRST AID

Eye Contact: In case of contact, immediately flush eyes with plenty of water. Remove contact lenses and flush again. Get medical attention if irritation persists.

Skin Contact: In case of contact, immediately flush skin with plenty of water. Remove contaminated clothing and shoes. Get medical attention if irritation persists. Wash clothing before reuse. Clean shoes thoroughly before reuse.

Inhalation: No special measures required. Treat symptomatically.

Ingestion: Get medical attention if symptoms occur.

Principal display panel and representative label

ECOLAB

Io-Shield™

Iodine Barrier Teat Dip

An aid in reducing the spread of organisms which may cause mastitis

Contains an emollient system (glycerin and sorbitol) 6%

ACTIVE INGREDIENT:

Iodine. . . . . . . . . . . . . . . . . . . . . . . . . . . . . . . 0.25%

INERT INGREDIENTS:. . . . . . . . . . . . . . . 99.75%

TOTAL:. . . . . . . . . . . . . . . . . . . . . . . . . . . . 100.00%

208 L (55 US gal)

6300423

Ecolab · 370 Wabasha Street N · St Paul MN 55102-1390 USA · tel. 1 800 392 3392

© 2011 Ecolab USA · All rights reserved

Made in United States

www.ecolab.com · 701703/5300/1111